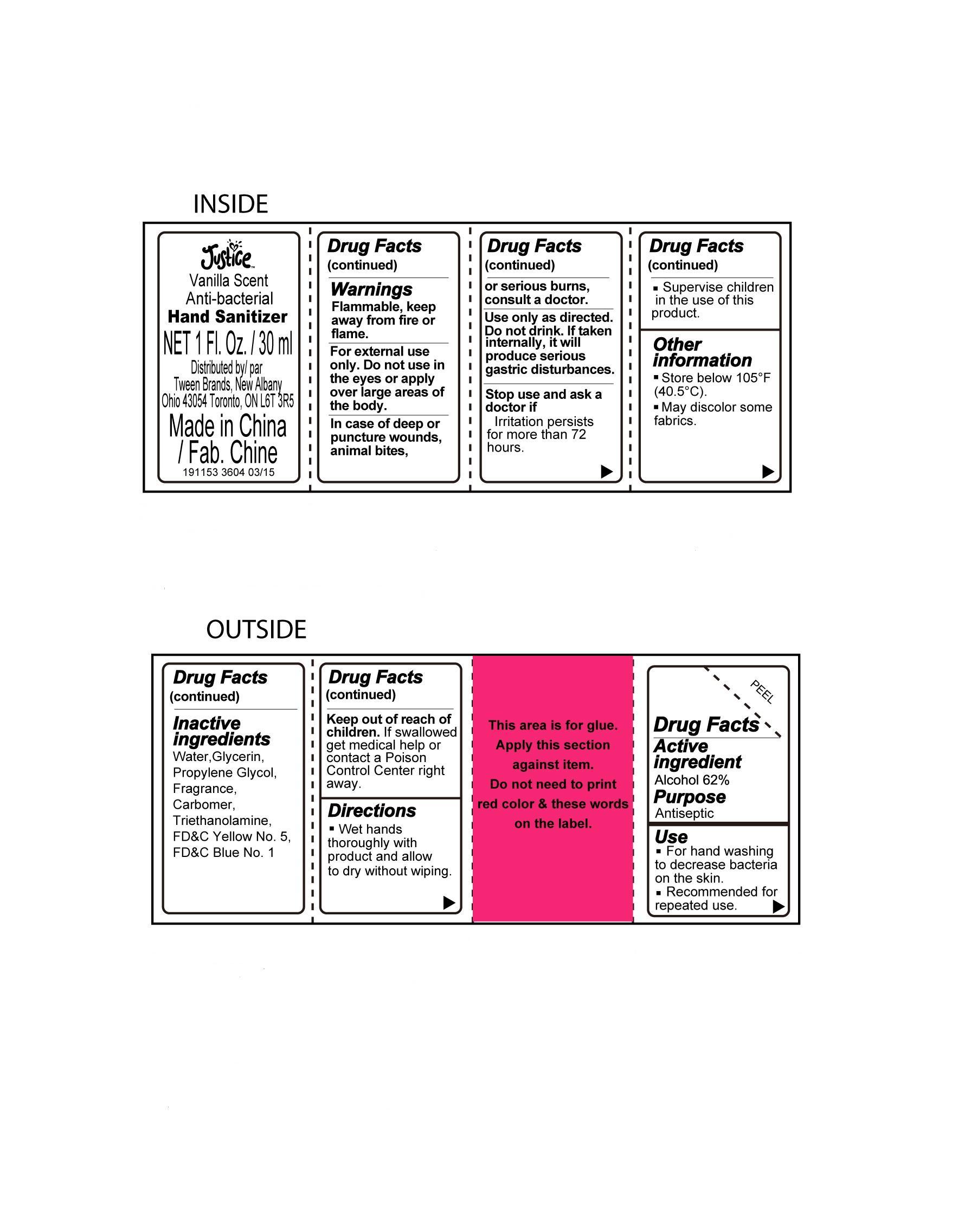 DRUG LABEL: Justice Vanilla Scent Anti-bacterial Hand Sanitizer
NDC: 60637-021 | Form: LIQUID
Manufacturer: Tween Brands Inc
Category: otc | Type: HUMAN OTC DRUG LABEL
Date: 20150127

ACTIVE INGREDIENTS: ALCOHOL 62 g/100 mL
INACTIVE INGREDIENTS: WATER; CARBOMER INTERPOLYMER TYPE A (ALLYL SUCROSE CROSSLINKED); GLYCERIN; PROPYLENE GLYCOL; TROLAMINE; FD&C YELLOW NO. 5; FD&C BLUE NO. 1

Active ingredient

Alcohol 62%

Purpose

Antiseptic

Use

■ For hand washing to decrease bacteria on the skin

■ Recommended for repeated use

Warnings

Flammable, keep away from fire or flame.

For external use only. Do not use in the eyes or apply over large areas of the body.

In case of deep or puncture wounds, animal bites, or serious burns, consult a doctor.

Use only as directed. Do not drink. If taken internally, it will produce serious gastric disturbances.

Stop use and ask a doctor if

■ Irritation persists for more than 72 hours.

■ Supervise children in the use of this product.

Keep out of reach of children

If swallowed get medical help or contact a Poison Control Center right away.

Directions

Wet hands thoroughly with product and allow to dry without wiping.

Other information

■ Store below 105F(40.5C) ■ May discolor some fabrics

Inactive ingredients

Water, Glycerin, Propylene Glycol, Fragrance, Carbomer, Triethanolamine, FD&C Yellow No.5,FD&C Blue No.1